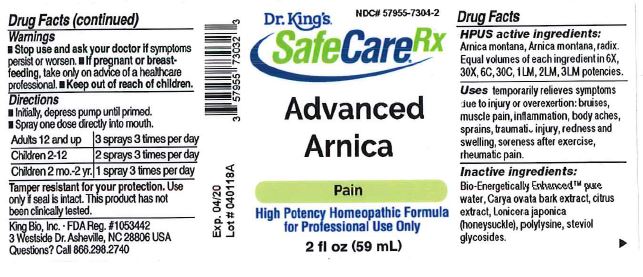 DRUG LABEL: Advanced Arnica
NDC: 57955-7304 | Form: LIQUID
Manufacturer: King Bio Inc.
Category: homeopathic | Type: HUMAN OTC DRUG LABEL
Date: 20180531

ACTIVE INGREDIENTS: ARNICA MONTANA 6 [hp_X]/59 mL; ARNICA MONTANA ROOT 6 [hp_X]/59 mL
INACTIVE INGREDIENTS: WATER; CARYA OVATA BARK; CITRUS BIOFLAVONOIDS; LONICERA JAPONICA FLOWER; POLYEPSILON-LYSINE (4000 MW); REBAUDIOSIDE A

Advanced Arnica

Drug Facts

____________________________________________________________________________________________________________________

HPUS active ingredients: Arnica montana, Arnica montana, radix . Equal volumes of each ingredient in 6X, 30X, 6C, 30C, 1LM, 2LM, 3LM potencies.

INDICATIONS AND USAGE

Uses temporarily relieves symptoms due to injury or overexertion: bruises, muscle pain, inflammation, body aches, sprains, traumatic injury, redness and swelling, soreness after exercise, rheumatic pain.

INACTIVE INGREDIENT

Inactive ingredients: Bio-Energetically Enhanced pure water, Carya ovata bak extract, citrus extract, Lonicera japonica (honeysuckle), polylysine, steviol glycosides.

Warnings

- Stop use and ask your doctor if symptoms persist or worsen.
- If pregnant or breast-feeding, take only on advice of a healthcare professional.

- Keep out of reach of children.

Directions:

- Initially, depress pump until primed.
- Spray one dose directly into mouth.
- Adults 12 and up: 3 sprays 3 times per day.
- Children 2-12 : 2 sprays 3 times per day.
- Children 2 mo-2 yr: 1 spray 3 times per day.

OTHER SAFETY INFORMATION

Tamper resistant for your protection. Use only if safety seal is intact. This product has not been clinically tested.

PURPOSE

Uses temporarily relieves symptoms due to injury or overexertion:

- bruises
- muscle pain
- inflammation
- body aches
- sprains
- traumatic injury
- redness and swelling
- soreness after exercise
- rheumatic pain